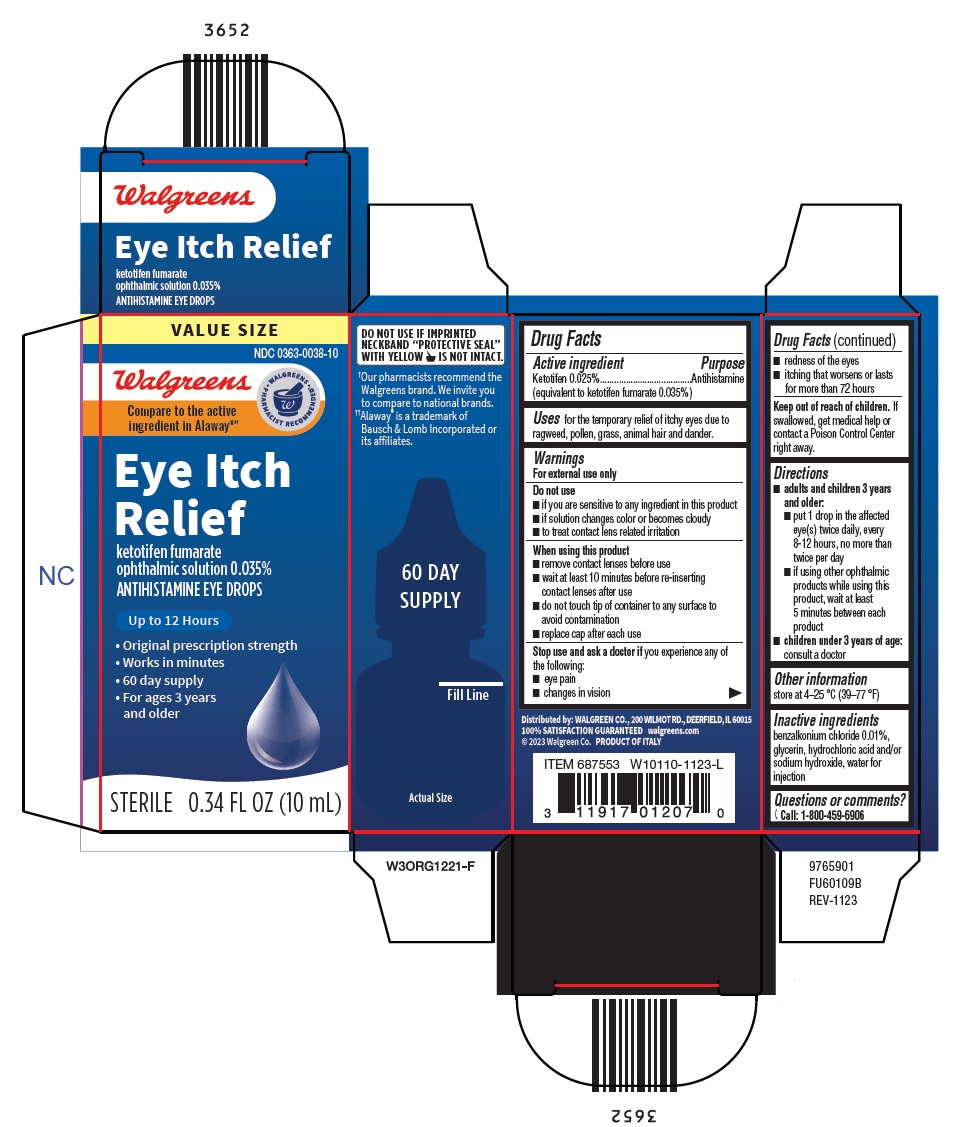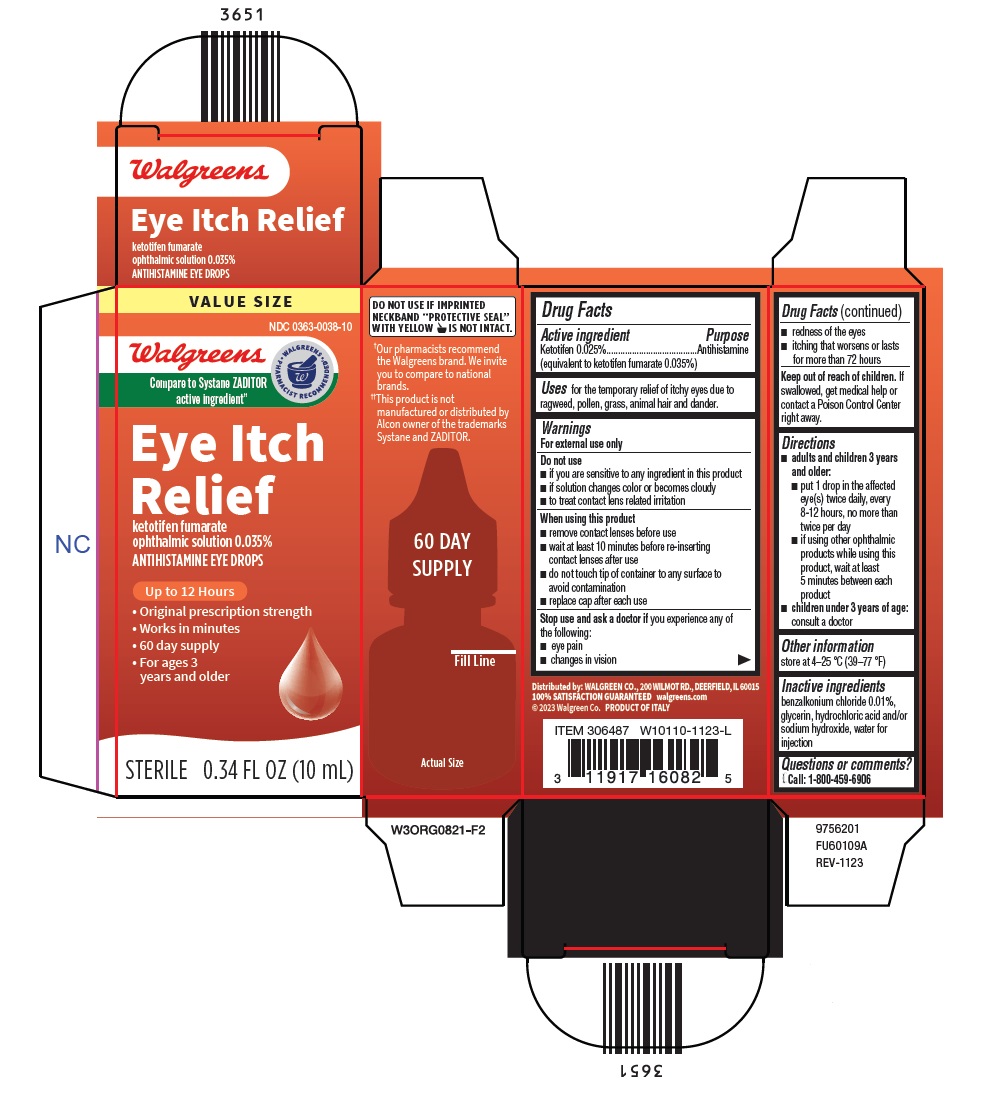 DRUG LABEL: Eye Itch Relief
NDC: 0363-0038 | Form: SOLUTION
Manufacturer: Walgreen Company
Category: otc | Type: HUMAN OTC DRUG LABEL
Date: 20260114

ACTIVE INGREDIENTS: KETOTIFEN FUMARATE 0.35 mg/1 mL
INACTIVE INGREDIENTS: BENZALKONIUM CHLORIDE; GLYCERIN; HYDROCHLORIC ACID; SODIUM HYDROXIDE; WATER

Drug Facts

Active ingredient

Ketotifen 0.025%
(equivalent to ketotifen fumarate 0.035%)

Purpose

Antihistamine

Uses

for the temporary relief of itchy eyes due to ragweed, pollen, grass, animal hair and dander.

Warnings

For external use only

Do not use

■ if you are sensitive to any ingredient in this product

■ if solution changes color or becomes cloudy

■ to treat contact lens related irritation

When using this product

■ remove contact lenses before use

■ wait at least 10 minutes before re-inserting content lenses after use

■ do not touch tip of container to any surface to avoid contamination

■ replace cap after each use

Stop use and ask a doctor ifyou experience any of the following:

■ eye pain

■ changes in vision

■ redness of the eyes

■ itching that worsens or lasts for more than 72 hours

Keep out of reach of children.

If swallowed, get medical help or contact a Poison Control Center right away.

Directions

- adults and children 3 years and older.
  - put 1 drop in the affected eye(s) twice daily, every 8-12 hours, no more than twice per day
  - if using other ophthalmic products while using this product, wait at least 5 minutes between each product
- children under 3 years of age: consult a doctor

Other information

store at 4-25 °C (39-77 °F)

Inactive ingredients

benzalkonium chloride 0.01%, glycerin, hydrochloric acid and/or sodium hydroxide, water for injection

Questions or comments?

{phone icon} Call: 1-800-459-6906

Distributed by: WALGREEN CO., 200 WILMOT RD., DEERFIELD, IL 60015
100% SATISFACTION GUARANTEED walgreens.com
© 2023 Walgreen Co. PRODUCT OF ITALY

Package/Label Principal Display Panel

VALUE SIZE

NDC 0363-0038-10

Walgreens

Compare to Systane ZADITOR active ingredient††

Eye Itch
Relief

ketotifen fumarate
ophthalmic solution 0.035%
ANTIHISTAMINE EYE DROPS

Up to 12 Hours

- Original prescription strength
- Works in minutes
- 60 day supply
- For ages 3
- years and older
- STERILE 0.34 FL OZ (10 mL)
- 9756201

Package/Label Principal Display Panel

VALUE SIZE

NDC 0363-0038-10

Walgreens
Compare to the active
ingredient in Alaway®††

Eye Itch
Relief
ketotifen fumarate
ophthalmic solution 0.035%
ANTIHISTAMINE EYE DROPS

Up to 12 Hours

- Original prescription strength
- Works in minutes
- 60 day supply
- For ages 3 years
  and older
- STERILE 0.34 FL OZ (10 mL)
- 9765901